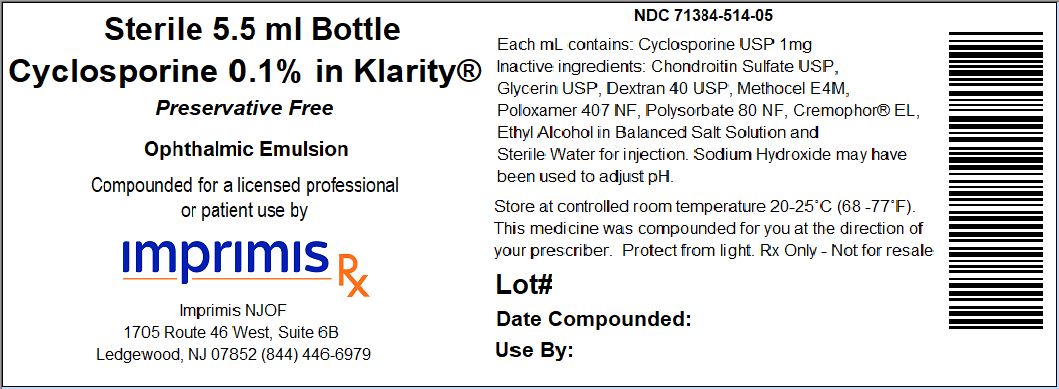 DRUG LABEL: Cyclosporine/Chondroitin PF
NDC: 71384-514 | Form: EMULSION
Manufacturer: Imprimis NJOF, LLC
Category: prescription | Type: HUMAN PRESCRIPTION DRUG LABEL
Date: 20200210

ACTIVE INGREDIENTS: CYCLOSPORINE 1 mg/1 mL

STORAGE AND HANDLING

Store at 20° to 25° C (68° to 77° F)